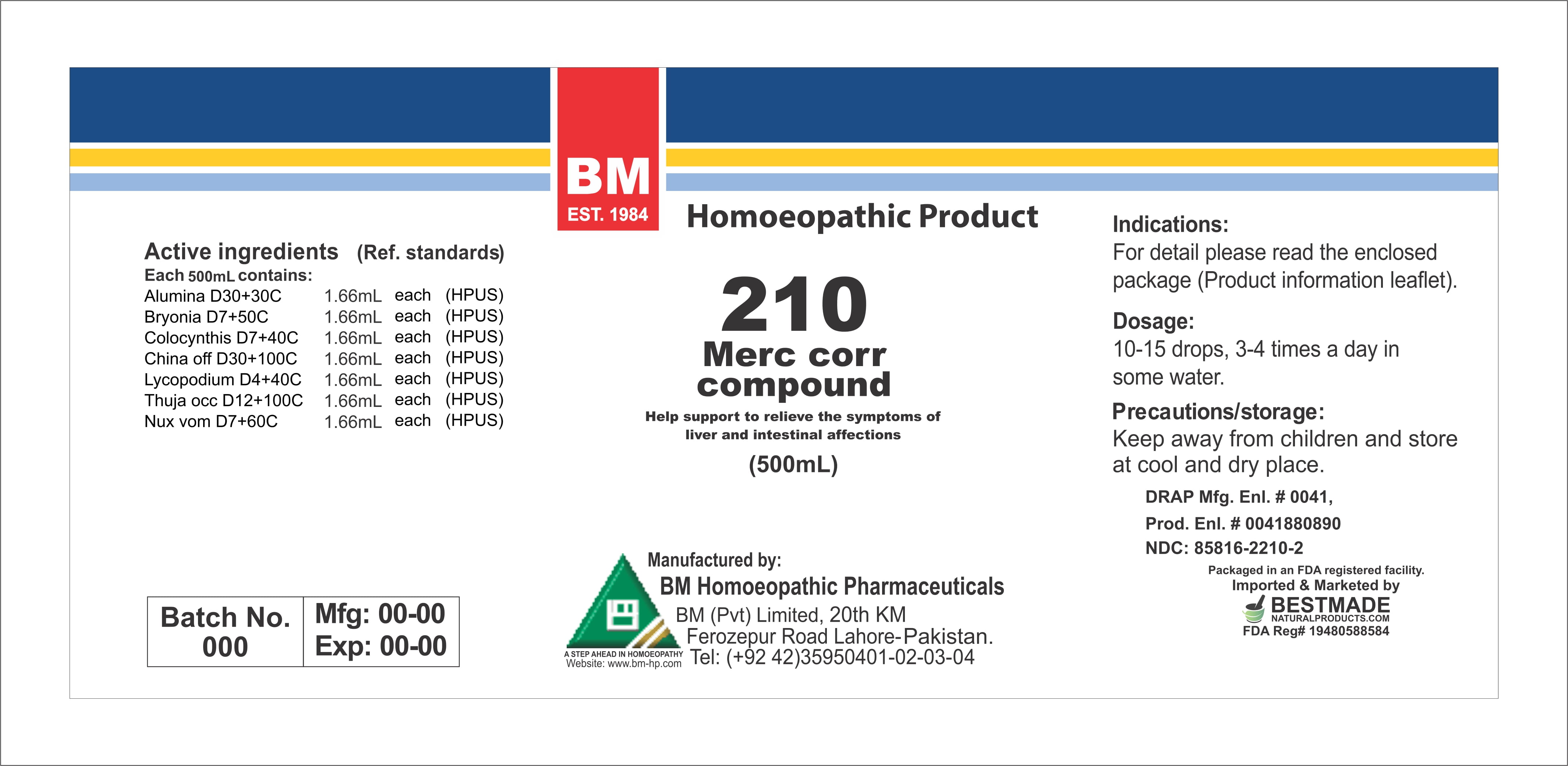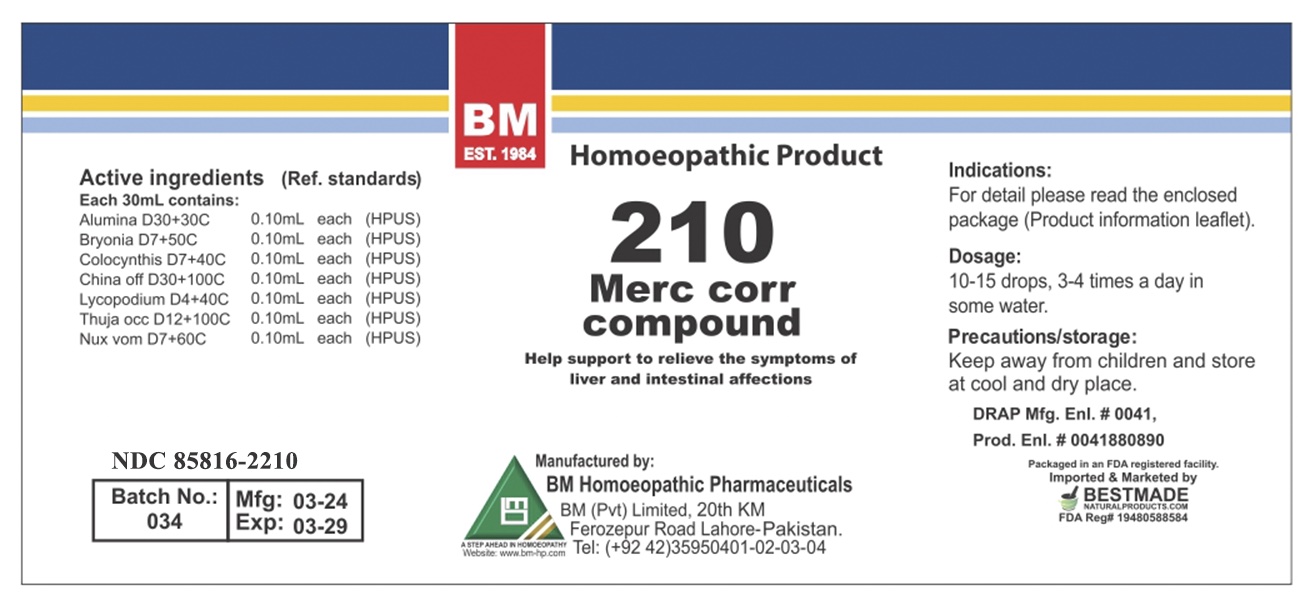 DRUG LABEL: MERC CORR
NDC: 85816-2210 | Form: LIQUID
Manufacturer: BM Private Limited
Category: homeopathic | Type: HUMAN OTC DRUG LABEL
Date: 20260212

ACTIVE INGREDIENTS: ALUMINA 30 [hp_X]/1 mL; STRYCHNOS NUX-VOMICA SEED 7 [hp_X]/1 mL; THUJA OCCIDENTALIS LEAFY TWIG 12 [hp_X]/1 mL; LYCOPODIUM CLAVATUM SPORE 4 [hp_X]/1 mL; BRYONIA ALBA ROOT 7 [hp_X]/1 mL; CITRULLUS COLOCYNTHIS FRUIT PULP 7 [hp_X]/1 mL; CINCHONA OFFICINALIS BARK 30 [hp_X]/1 mL
INACTIVE INGREDIENTS: ALCOHOL 0.96 mL/1 mL

BM HOMEOPATHIC REMEDY LIQUIDS MERC CORR/ BM210

DOSAGE AND ADMINISTRATION

10-15 drops, 3-4 times a day in some water

ACTIVE INGREDIENT

alumina, bryonia, colocynthis, china off, lycopodium, thuja occ, nux vom

INACTIVE INGREDIENT

ALCOHOL

INDICATIONS AND USAGE

For detail, please read the enclosed package (product information leaflet)

PURPOSE

For detail, please read the enclosed package (product information leaflet)

KEEP OUT OF REACH OF CHILDREN

Precautions/storage:
Keep away from children and store at cool and dry place.

WARNINGS

Precautions/storage:
Keep away from children and store at cool and dry place.

Package 1:

Package 2: